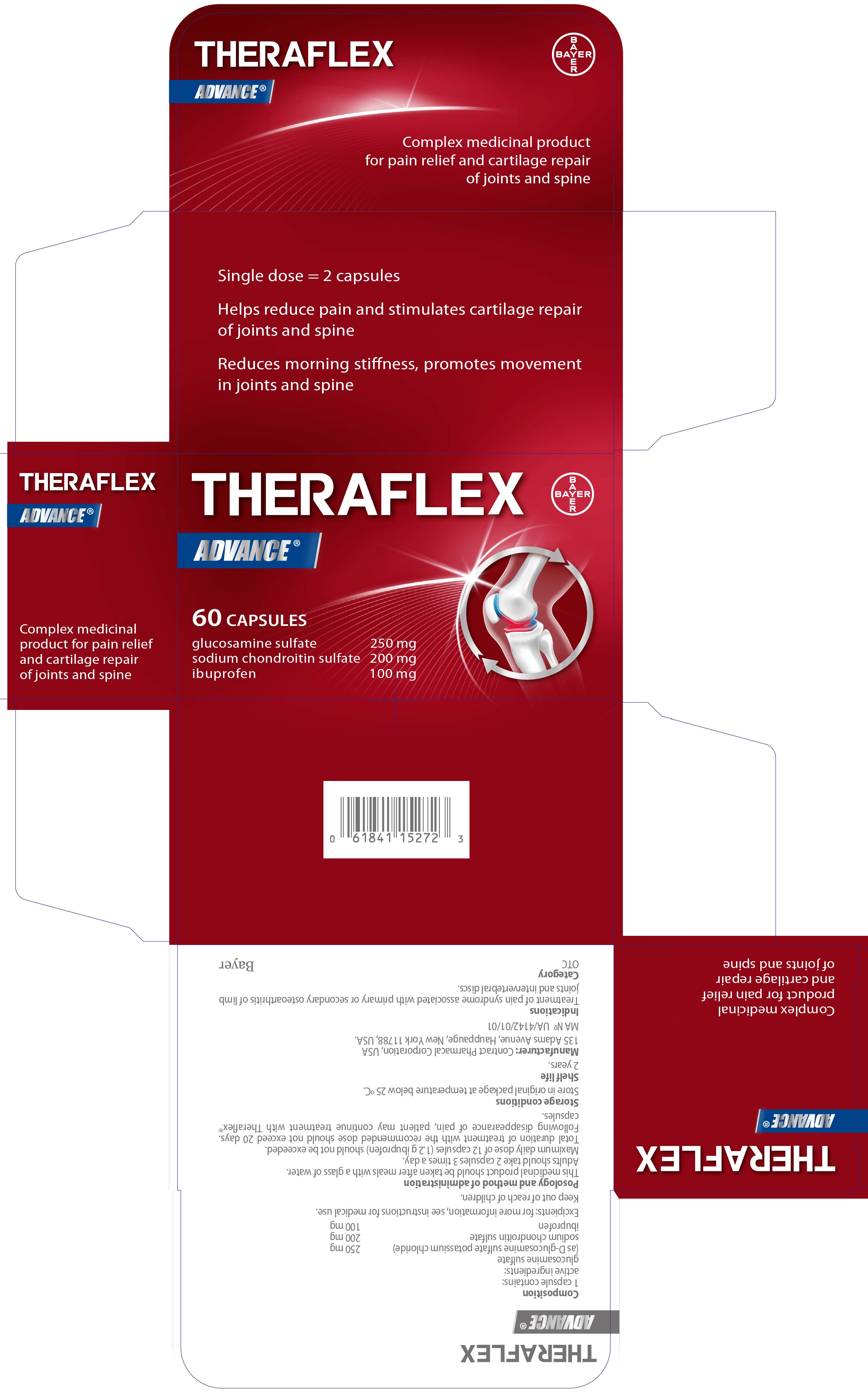 DRUG LABEL: Theraflex Advance
NDC: 61841-152 | Form: TABLET
Manufacturer: Bayer HealthCare LLC.
Category: otc | Type: HUMAN OTC DRUG LABEL
Date: 20260112

ACTIVE INGREDIENTS: IBUPROFEN 100 mg/1 1; GLUCOSAMINE SULFATE 250 mg/1 1; CHONDROITIN SULFATE (BOVINE) 200 mg/1 1
INACTIVE INGREDIENTS: STARCH, CORN; CROSPOVIDONE; GELATIN; MAGNESIUM STEARATE; CELLULOSE, MICROCRYSTALLINE; SILICON DIOXIDE; STEARIC ACID; TITANIUM DIOXIDE; FD&C BLUE NO. 1

Theraflex™ Advance

Drug Facts

ACTIVE INGREDIENT

PURPOSE

Active ingredients (in each capsule) | Purposes
Glucosamine Sulfate 250 mg | Dietary Supplement
Chondroitin Sulfate 200 mg | Dietary Supplement
Ibuprofen 100 mg | Analgesic

Uses

- temporarily relieves minor aches and pains associated with
  - backache
  - arthritis.

Warnings

Allergy alert

Ibuprofen may cause a severe allergic reaction wich may include:

- hives
- facial swelling
- asthma (wheezing)
- shock.

Alcohol warning

If you consume 3 or more alcoholic drinks every day, ask your doctor whether you should take ibuprofen or other pain relieves/fever reducers. Ibuprofen may cause stomach bleeding.

Do not use

- if you have ever had an allergic reaction to any other pain reliever/fever reducer.

When using this product

- take with food or milk if stomach upset occurs.

PREGNANCY OR BREAST FEEDING

I f pregnant or breast-feeding, ask a health professional before use.

Keep out of reach of children. In case of overdose, get medical help or contact a Poison Control Center right away.

PREGNANCY OR BREAST FEEDING

It is especially important not to use ibuprofen during the last 3 months of pregnancy unless specifically directed to do so by a doctor because it may cause problems in the unborn child or c omplications during delivery.

Directions

Adults

Take 1 capsule every 4 to 6 hours while symptoms persist. If pain or fever does not respond to 1 capsule, 2 capsules may be used, but do not exceed 6 capsules in 24 hours, unless directed by a doctor. The smallest effective dose should be used.

Children

Do not give this product to children under 12 unless directed by a doctor.

Do not exceed recommended dose.

Other information

- store at room temperature, USP.

Inactive ingredients

Corn Starch, Crospovidone, Gelatin, Magnesium Stearate, Microcrystalline Cellulose, Polyvinylpyrrolidone, Pregelatinized Starch, Silica, Sodium Starch Glycolate, Stearic Acid, Titanium Dioxide, FD&C Blue#1 Lake.

PRINCIPAL DISPLAY PANEL - 60 Capsule Bottle Carton

THERAFLEX™

ADVANCE

60 CAPSULES

Ibuprofen 100 mg
Glucosamine Sulfate 250 mg
Chondroitin Sulfate 200 mg